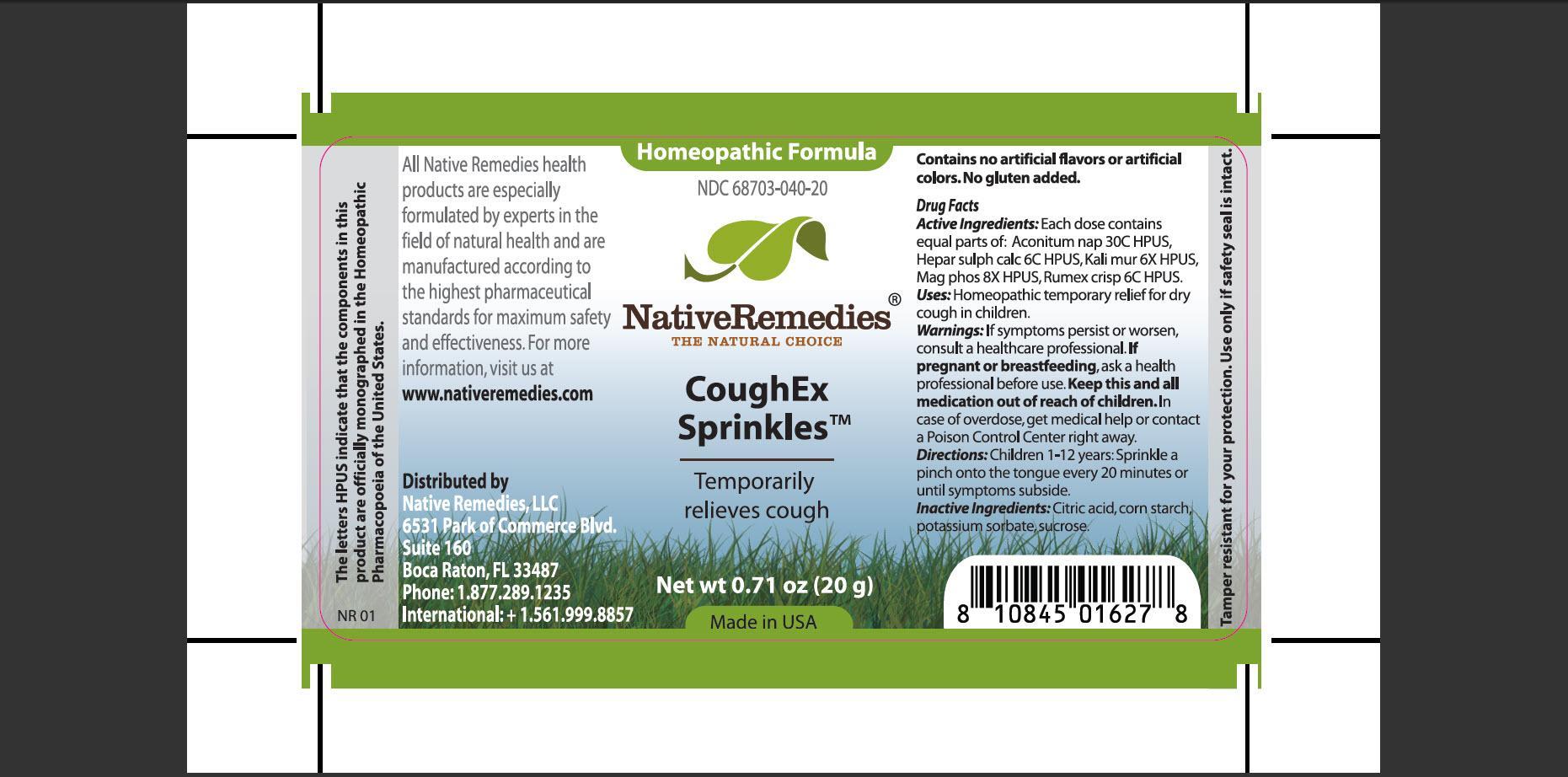 DRUG LABEL: CoughEx Sprinkles
NDC: 68703-040 | Form: GRANULE
Manufacturer: Native Remedies, LLC
Category: homeopathic | Type: HUMAN OTC DRUG LABEL
Date: 20121127

ACTIVE INGREDIENTS: ACONITUM NAPELLUS 30 [hp_C]/16 mg; CALCIUM SULFIDE 6 [hp_C]/16 mg; POTASSIUM CHLORIDE 6 [hp_X]/16 mg; MAGNESIUM PHOSPHATE, DIBASIC TRIHYDRATE 8 [hp_X]/16 mg; RUMEX CRISPUS ROOT 6 [hp_C]/16 mg
INACTIVE INGREDIENTS: CITRIC ACID MONOHYDRATE; STARCH, CORN; POTASSIUM SORBATE; SUCROSE

CoughEx Sprinkles

PURPOSE

Temporarily relieves cough

ACTIVE INGREDIENT

Active Ingredients: Each dose contains equal parts of: Aconitum nap 30C HPUS, Hepar sulph calc 6C HPUS, Kali mur 6X HPUS, Mag phos 8X HPUS, Rumex crisp 6C HPUS.

INDICATIONS AND USAGE

Uses: Homeopathic temporary relief for dry cough in children.

WARNINGS

Warnings: If symptoms persist or worsen, consult a healthcare professional.

PREGNANCY OR BREAST FEEDING

If pregnant or breastfeeding, ask a health professional before use.

KEEP OUT OF REACH OF CHILDREN

Keep this and all medication out of reach of children.

OVERDOSAGE

In case of overdose, get medical help or contact a Poison Control Center right away.

DOSAGE AND ADMINISTRATION

Directions: Children 1-12 years: Sprinkle a pinch onto the tongue every 20 minutes or until symptoms subside.

INACTIVE INGREDIENT

Inactive Ingredients: Citric acid, corn starch, potassium sorbate, sucrose.

PATIENT COUNSELING INFORMATION

The letters HPUS indicate that the components in this product are officially monographed in the Homeopathic Pharmacopoeia of the United States.

All Native Remedies health products are especially formulated by experts in the field of natural health, and are manufactured according to the highest pharmaceutical standards for maximum safety and effectiveness. For more information, visit us at www.nativeremedies.com

Distributed by
Native Remedies, LLC
6531 Park of Commerce Blvd
Suite 160
Boca Raton, FL 33487
Phone: 1.877.289.1235
International: +1.561.999.8857

Contain no artificial flavors or artificial colors. No gluten added.

STORAGE AND HANDLING

Tamper resistant seal for your protection. Use only if safety seal is intact.